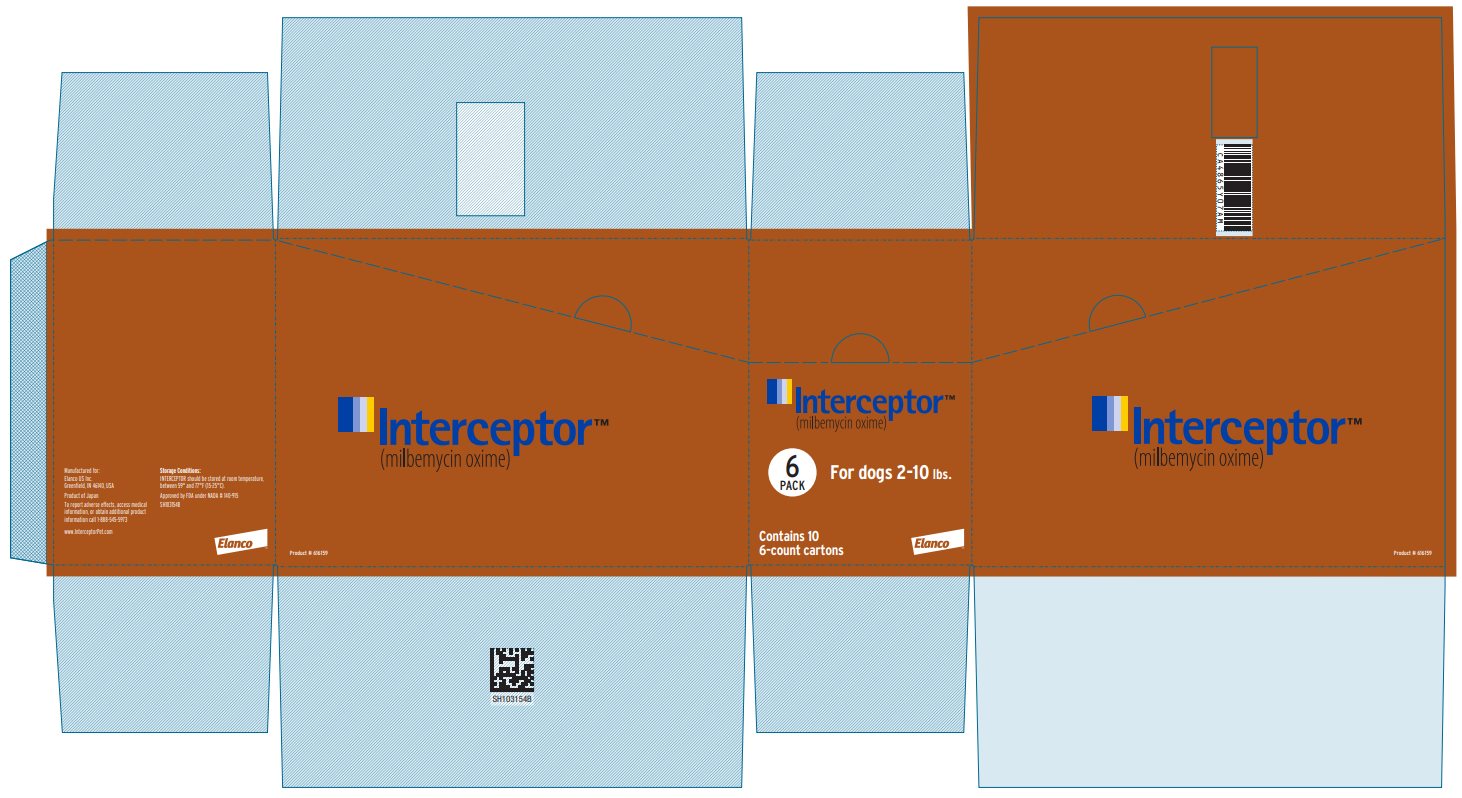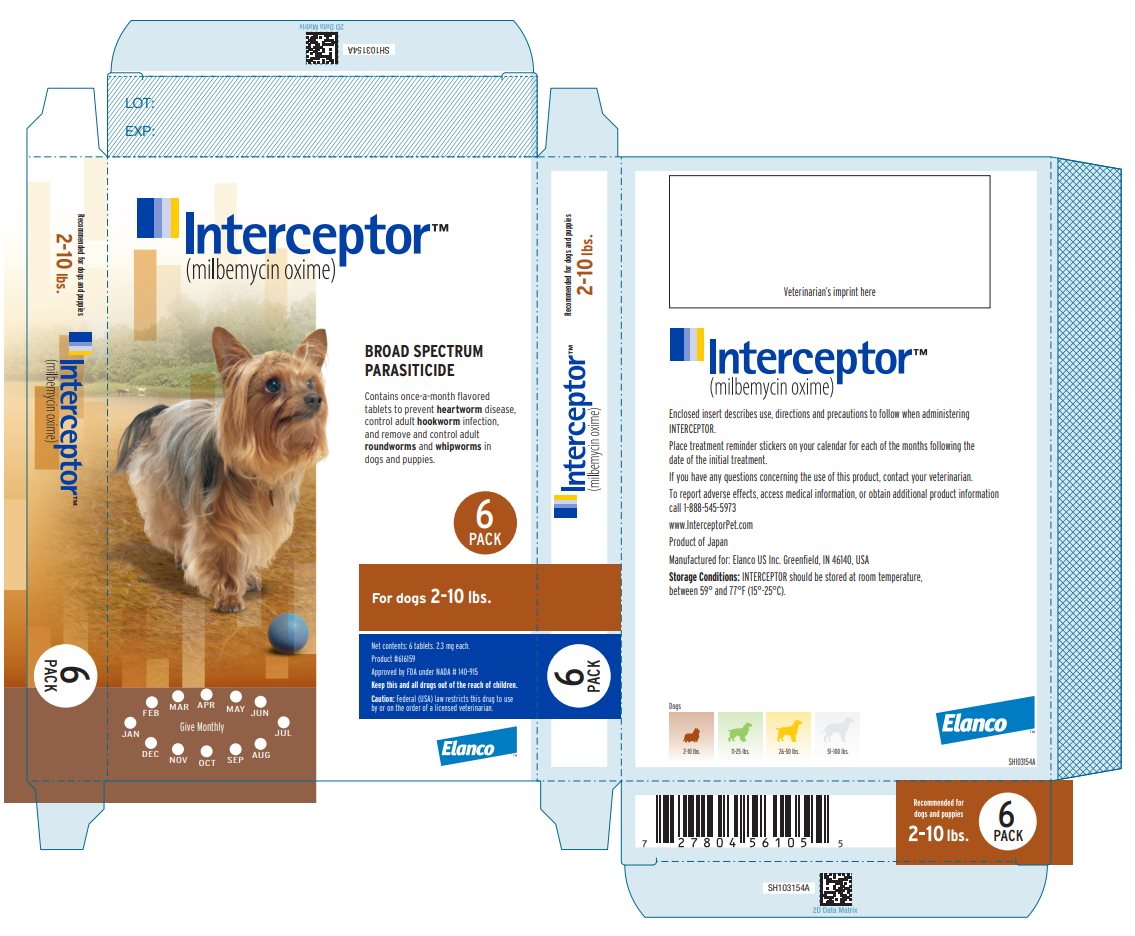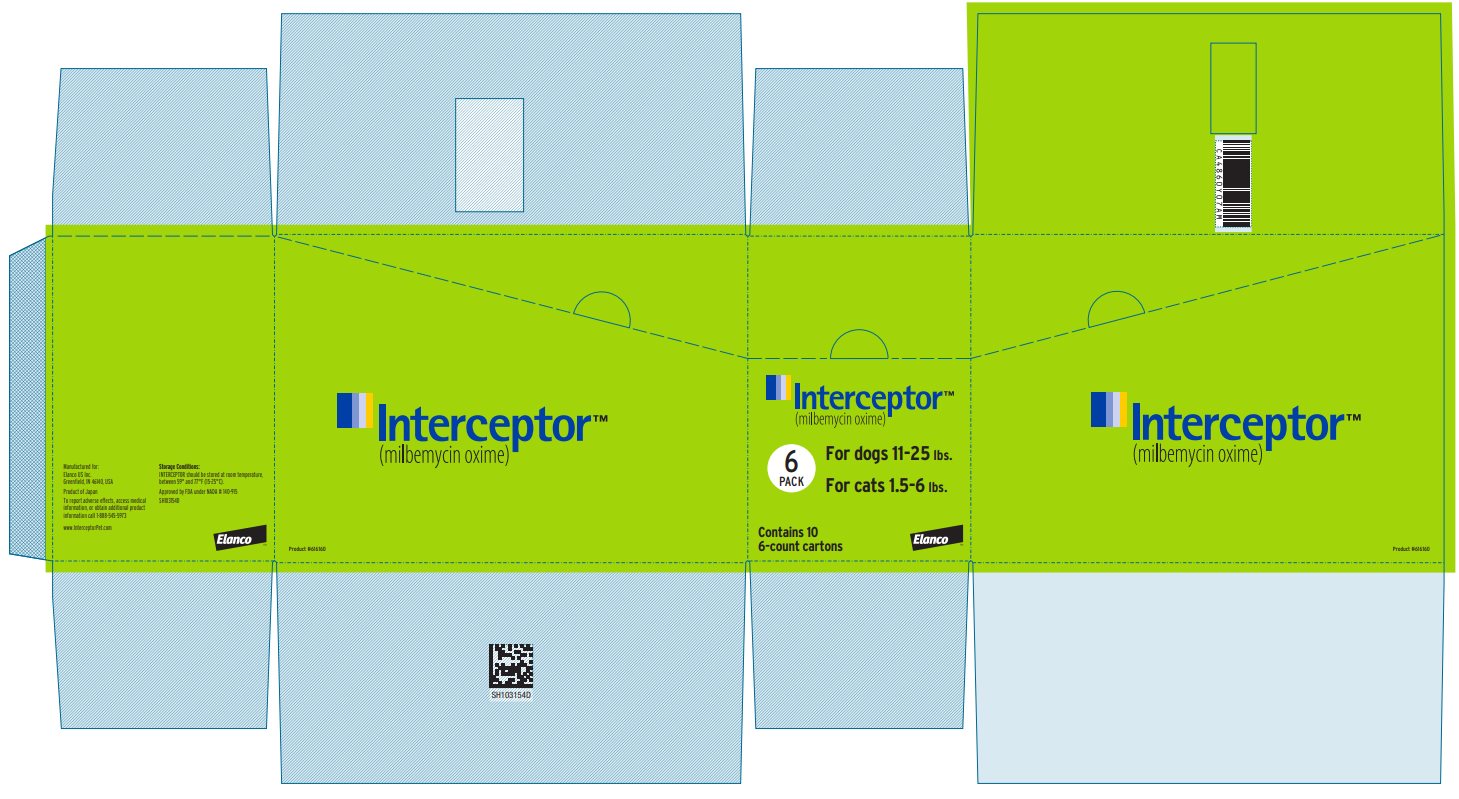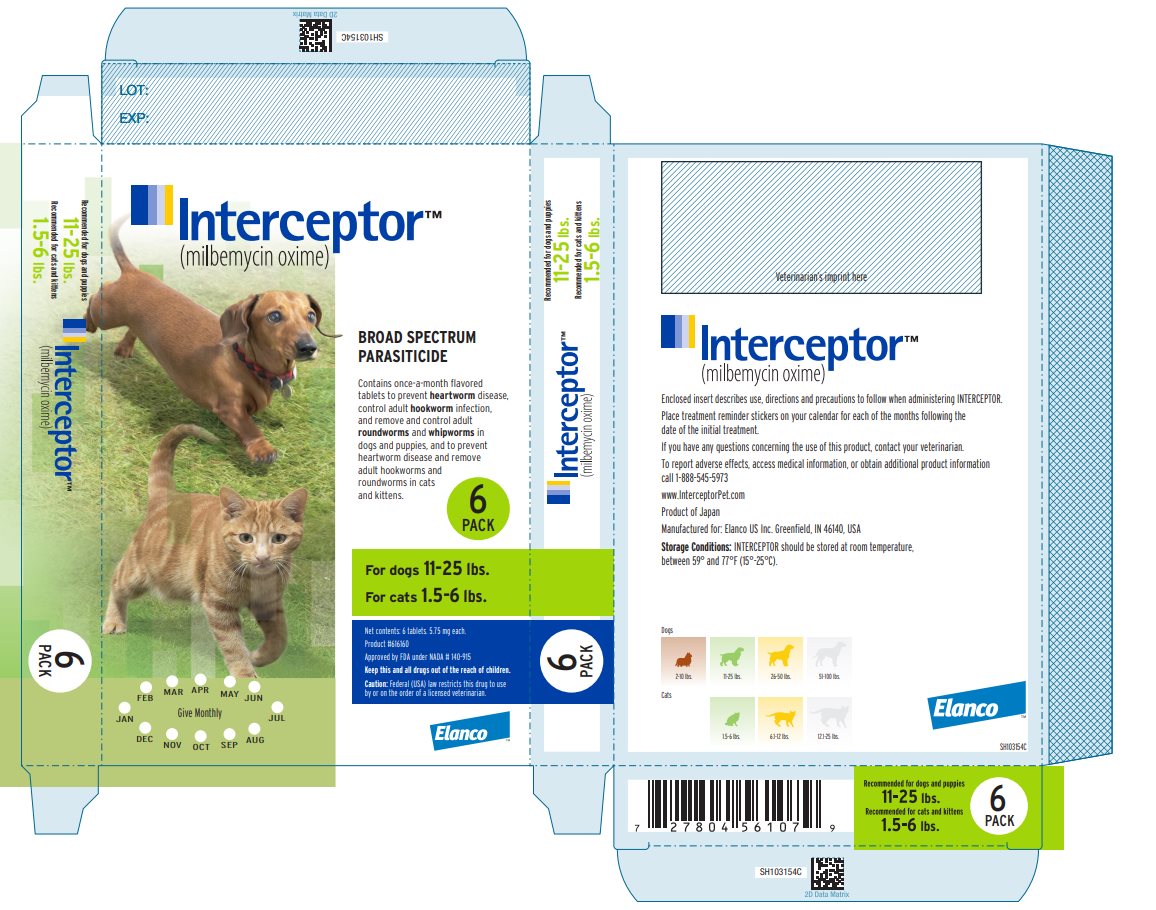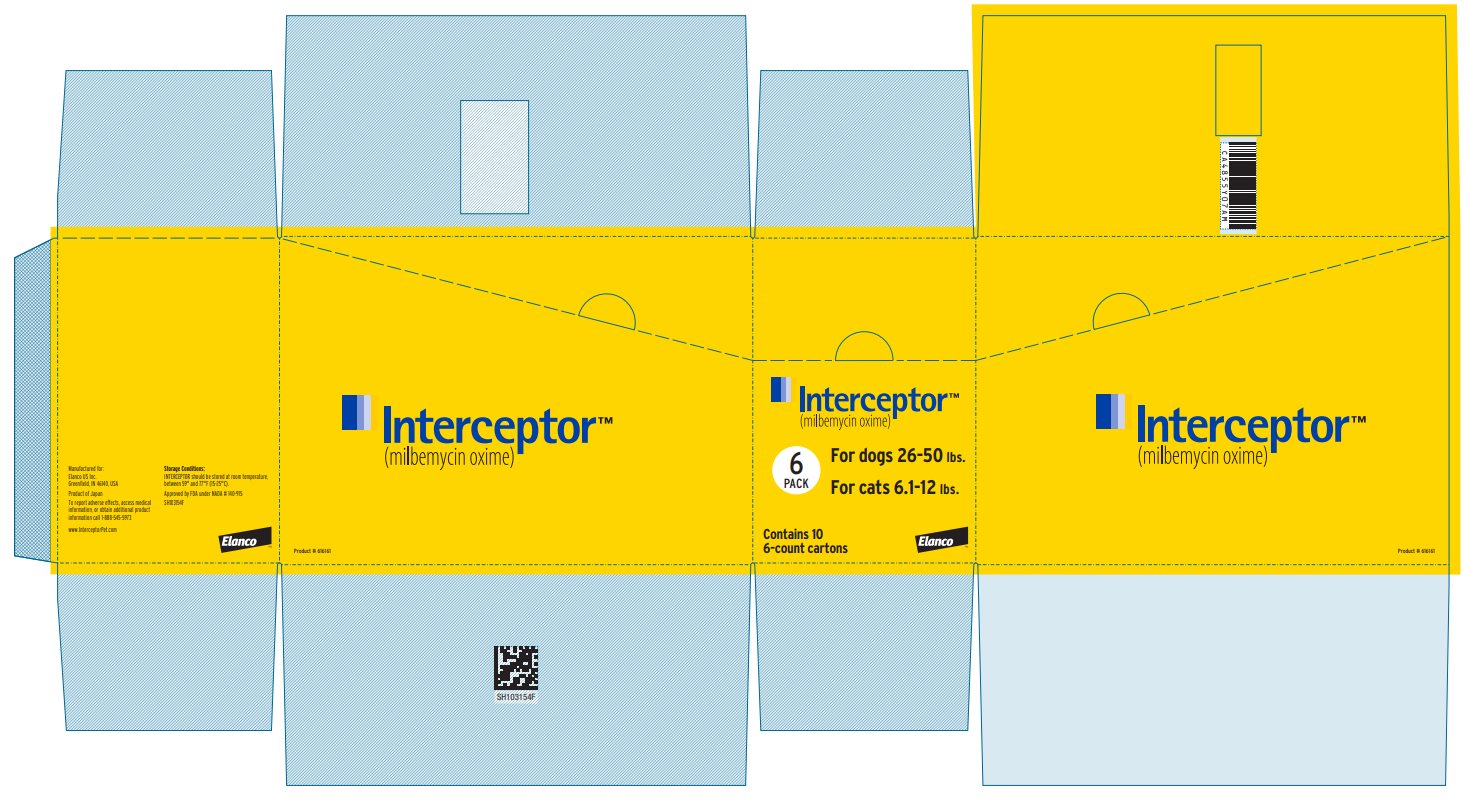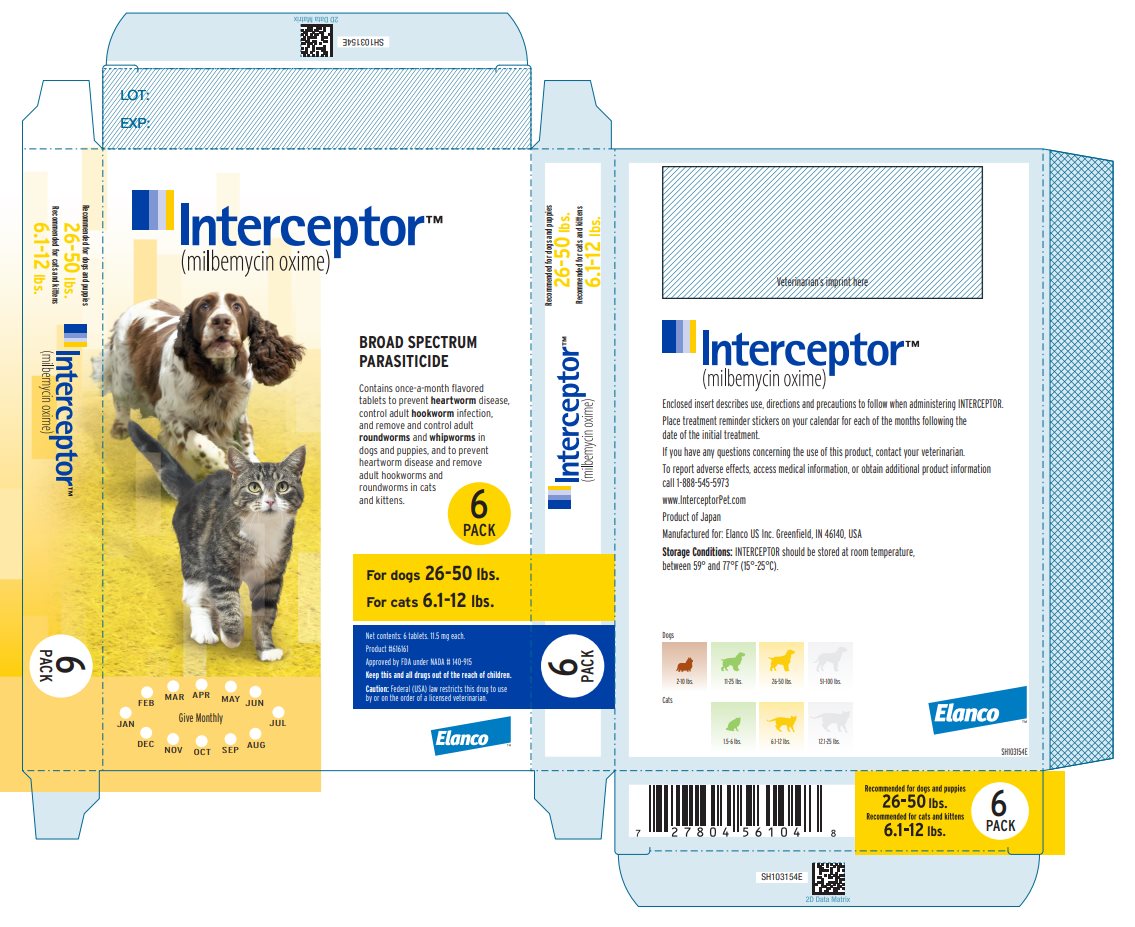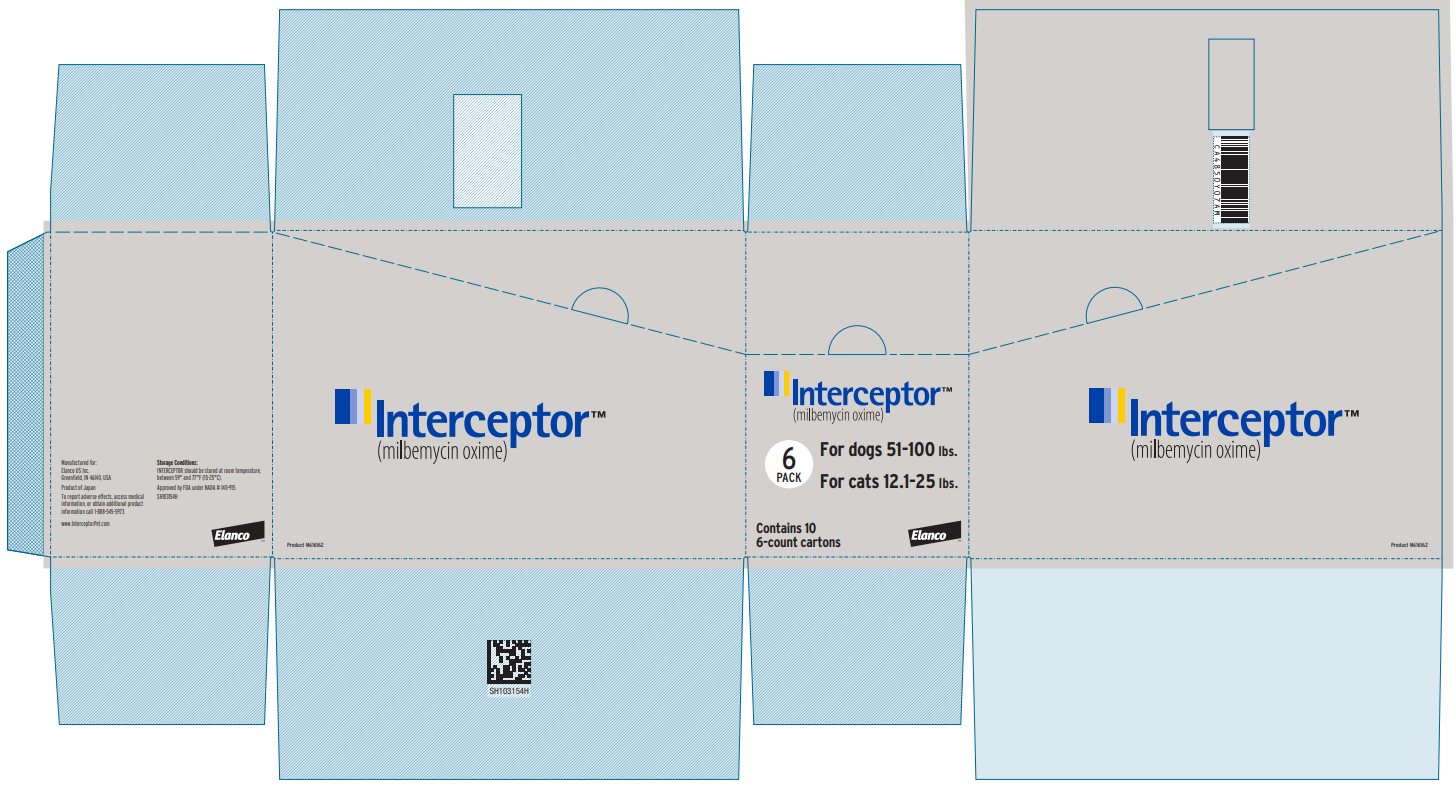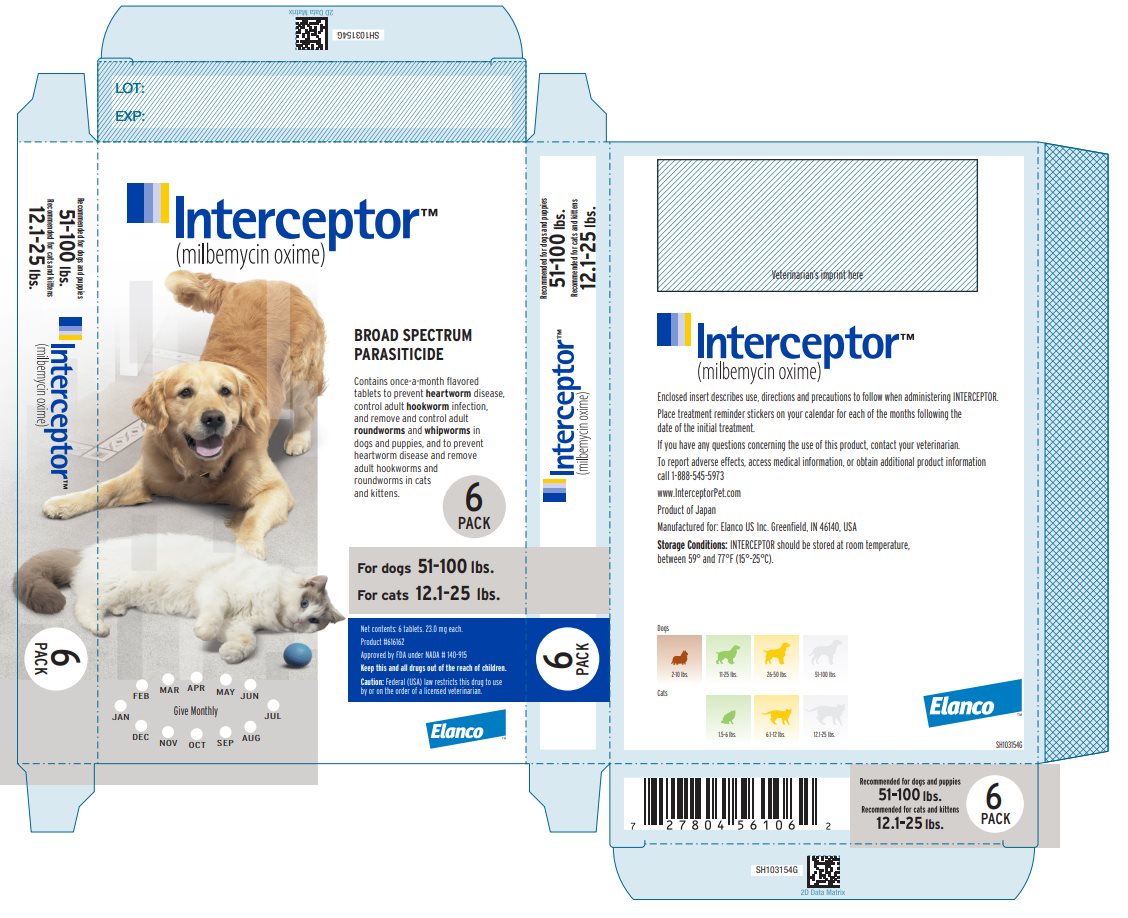 DRUG LABEL: Interceptor Flavor Tabs
NDC: 58198-2011 | Form: TABLET
Manufacturer: Elanco US Inc.
Category: animal | Type: PRESCRIPTION ANIMAL DRUG LABEL
Date: 20240606

ACTIVE INGREDIENTS: Milbemycin Oxime 2.3 mg/1 1

Interceptor™

(milbemycin oxime)

INFORMATION FOR DOSING DOGS

The palatable once-a-month tablet that prevents heartworm disease, controls adult hookworm, and removes and controls adult roundworm and whipworm infections in dogs and puppies.

Caution:

Federal (USA) law restricts this drug to use by or on the order of a licensed veterinarian. Keep this and all drugs out of the reach of children.

Description:

INTERCEPTOR is available in four tablet sizes in color-coded packages for oral administration to dogs and puppies. Each tablet is formulated to provide a minimum of 0.23 mg/lb (0.5 mg/kg) body weight of milbemycin oxime. Milbemycin oxime consists of the oxime derivatives of 5-didehydromilbemycins in the ratio of approximately 80% A4 (C32H45NO7, MW 555.71) and 20% A3 (C31H43NO7, MW 541.68).

Package color | Milbemycin oxime tablet
Brown | 2.3 mg*
Green | 5.75 mg
Yellow | 11.5 mg
White | 23.0 mg
*for dogs only

Indications:

INTERCEPTOR is indicated for use in the prevention of heartworm disease caused by Dirofilaria immitis, the control of adult Ancylostoma caninum (hookworm), and the removal and control of adult Toxocara canis and Toxascaris leonina (roundworms) and Trichuris vulpis (whipworm) infections in dogs and in puppies four weeks of age or greater and two pounds body weight or greater.

Dosage:

INTERCEPTOR is given orally, once a month, at the recommended minimum dosage rate of 0.23 mg milbemycin oxime per pound of body weight (0.5 mg/kg).

Recommended Dosage Schedule for Dogs
Body Weight | INTERCEPTOR
2-10 lbs. | One tablet (2.3 mg)
11-25 lbs. | One tablet (5.75 mg)
26-50 lbs. | One tablet (11.5 mg)
51-100 lbs. | One tablet (23.0 mg)

Dogs over 100 lbs. are provided the appropriate combination of tablets.

Administration:

INTERCEPTOR is palatable and most dogs will consume the tablet willingly when offered by the owner. As an alternative, the dual-purpose tablet may be offered in food or administered as other tablet medications. Watch the dog closely following dosing to be sure the entire dose has been consumed. If it is not entirely consumed, redose once with the full recommended dose as soon as possible.

INTERCEPTOR must be administered monthly, preferably on the same date each month. The first dose should be administered within one month of the dog's first exposure to mosquitoes and monthly thereafter until the end of the mosquito season. If a dose is missed and a 30-day interval between dosing is exceeded, administer INTERCEPTOR immediately and resume the monthly dosing schedule.

If INTERCEPTOR replaces diethylcarbamazine (DEC) for heartworm prevention, the first dose must be given within 30 days after the last dose of DEC.

Palatability:

Palatability trials conducted in 244 dogs from 10 different U.S. veterinary practices demonstrated that INTERCEPTOR was willingly accepted from the owner by over 95% of dogs. The trial was comprised of dogs representing 60 different breeds and both sexes, with weights ranging from 2.1 lbs. to 143.3 lbs., and ages ranging from 8 weeks to 15 years.

Precautions:

Do not use in puppies less than four weeks of age or less than two pounds of body weight. Prior to initiation of the INTERCEPTOR treatment program, dogs should be tested for existing heartworm infections. Infected dogs should be treated to remove adult heartworms and microfilariae prior to initiating treatment with INTERCEPTOR. Mild, transient hypersensitivity reactions manifested as labored respiration, vomiting, salivation and lethargy, have been noted in some treated dogs carrying a high number of circulating microfilariae. These reactions are presumably caused by release of protein from dead or dying microfilariae.

Adverse Reactions:

The following adverse reactions have been reported following the use of INTERCEPTOR: Depression/lethargy, vomiting, ataxia, anorexia, diarrhea, convulsions, weakness and hypersalivation.

Efficacy:

INTERCEPTOR eliminates the tissue stage of heartworm larvae and the adult stage of hookworm (Ancylostoma caninum), roundworms (Toxocara canis, Toxascaris leonina) and whipworm (Trichuris vulpis) infestations when administered orally according to the recommended dosage schedule.The anthelmintic activity of milbemycin oxime is believed to be a result of interference with invertebrate neurotransmission.

Safety:

Milbemycin oxime has been tested safely in over 75 different breeds of dogs, including collies, pregnant females, breeding males and females, and puppies over two weeks of age. In well-controlled clinical field studies, 786 dogs completed treatment with milbemycin oxime. Milbemycin oxime was used safely in animals receiving frequently used veterinary products such as vaccines, anthelmintics, antibiotics, steroids, flea collars, shampoos and dips.

Two studies in heartworm-infected dogs were conducted which demonstrated mild, transient hypersensitivity reactions in treated dogs with high microfilaremia counts (see Precautions for reactions observed). Safety studies in pregnant dogs demonstrated that high doses (1.5 mg/kg =3X) of milbemycin oxime given in an exaggerated dosing regimen (daily from mating through weaning), resulted in measurable concentrations of the drug in milk. Puppies nursing these females which received exaggerated dosing regimens demonstrated milbemycin-related effects. These effects were directly attributable to the exaggerated experimental dosing regimen. The product is normally intended for once-a-month administration only. Subsequent studies included using 3X daily from mating to one week before weaning and demonstrated no effects on the pregnant females or their litters. A second study where pregnant females were dosed once at 3X the monthly use rate either before, on the day of or shortly after whelping resulted in no effects on the puppies.

Some nursing puppies, at 2, 4, and 6 weeks of age, given greatly exaggerated oral milbemycin oxime doses (9.6 mg/kg = 19X) exhibited signs typified by tremors, vocalization and ataxia. These effects were all transient and puppies returned to normal within 24 to 48 hours. No effects were observed in puppies given the recommended dose of milbemycin oxime (0.5 mg/kg). This product has not been tested in dogs less than 1 kg weight.

A rising-dose safety study conducted in rough-coated collies, manifested a clinical reaction consisting of ataxia, pyrexia and periodic recumbency, in one of fourteen dogs treated with milbemycin oxime at 12.5 mg/kg (25X monthly use rate). Prior to receiving the 12.5 mg/kg dose (25X monthly use rate) on day 56 of the study, all animals had undergone an exaggerated dosing regimen consisting of 2.5 mg/kg milbemycin oxime (5X monthly use rate) on day 0, followed by 5.0 mg/kg (10X monthly use rate) on day 14 and 10.0 mg/kg (20X monthly use rate) on day 32. No adverse reactions were observed in any of the collies treated with this regimen up through the 10.0 mg/kg (20X monthly use rate) dose.

How supplied:

INTERCEPTOR is available in four tablet sizes (see Dosage section), formulated according to the weight of the dog. Each tablet size is available in color-coded packages of 6 or 12 tablets each, which are packaged 10 per display carton.

Storage conditions:

INTERCEPTOR should be stored at room temperature, between 59° and 77°F (15-25°C).

Interceptor™

(milbemycin oxime)

INFORMATION FOR DOSING CATS

The palatable once-a-month tablet that prevents heartworm disease and removes adult roundworms and hookworms in cats and kittens.

Caution:

Federal (USA) law restricts this drug to use by or on the order of a licensed veterinarian. Keep this and all drugs out of the reach of children.

Description:

INTERCEPTOR for Cats is available in three tablet sizes in color-coded packages for oral administration to cats and kittens. Each tablet is formulated to provide a minimum of 0.9 mg/lb (2.0 mg/kg) body weight of milbemycin oxime. Milbemycin oxime consists of the oxime derivatives of 5-didehydromilbemycins in the ratio of approximately 80% A4 (C32H45NO7, MW 555.71) and 20% A3 (C31H43NO7, MW 541.68).

Indications:

INTERCEPTOR for Cats is indicated for use in the prevention of heartworm disease caused by Dirofilaria immitis, and the removal of adult Ancylostoma tubaeforme (hookworm) and Toxocara cati (roundworm) in cats and kittens six weeks of age or greater and 1.5 lbs. body weight or greater.

Dosage:

INTERCEPTOR for Cats is given orally, once a month, at the recommended minimum dosage rate of 0.9 mg milbemycin oxime per pound of body weight (2.0 mg/kg).

Recommended Dosage Schedule for Cats
Body Weight | INTERCEPTOR
1.5 to 6 lbs. | One tablet (5.75 mg)
6.1-12 lbs. | One tablet (11.5 mg)
12.1-25 lbs. | One tablet (23.0 mg)

Cats over 25 lbs. are provided the appropriate combination of tablets.

Administration:

INTERCEPTOR for Cats is palatable and may be offered by the owner as a treat. As an alternative, the tablet may be offered in food or administered as other tablet medications. The tablets can be broken for ease of administration. Watch the cat closely following dosing to be sure the entire dose has been consumed. If it is not entirely consumed, redose once with the full recommended dose as soon as possible.

INTERCEPTOR for Cats must be administered monthly, preferably on the same date each month. The first dose should be administered within one month of the cat's first exposure to mosquitoes and monthly thereafter until the end of the mosquito season. If a dose is missed and a 30-day interval between dosing is exceeded, administer INTERCEPTOR for Cats immediately and resume the monthly dosing schedule. It is recommended that cats be tested for existing heartworm infection prior to starting treatment with INTERCEPTOR for Cats (see Precautions).

Palatability:

Palatability trials conducted in 72 cats demonstrated that cats were successfully dosed with INTERCEPTOR for Cats by the owner when they either offered the tablet as a treat, placed the tablet in the cat's mouth or placed the tablet in the cat's food in 72% of cats. About 16% of the cats were dosed manually and 13% of the cats were not successfully dosed according to the protocol.

Precautions:

Do not use in kittens less than six weeks of age or less than 1.5 lbs. body weight. Safety in heartworm-positive cats has not been established. Safety in breeding, pregnant, and lactating queens and breeding toms has not been established.

Efficacy:

INTERCEPTOR for Cats eliminate the tissue stage of heartworm larvae and hookworm (Ancylostoma tubaeforme) and roundworm (Toxocara cati) infections when administered orally according to the recommended dosage schedule.The anthelmintic activity of milbemycin oxime is believed to be a result of interference with invertebrate neuro- transmission.

Safety:

Milbemycin oxime has been tested safely in over 8 different breeds of cats. In well-controlled clinical field studies 141 cats completed treatment with milbemycin oxime. Milbemycin oxime was used safely in animals receiving frequently used veterinary products such as vaccines, anthelmintics, anesthetics, antibiotics, steroids, flea collars, shampoos and dips.

Safety studies were conducted in young cats and kittens and doses of 1X, 3X and 5X the minimum recommended dose of 2.0 mg/kg demonstrated no drug-related effects. Tolerability studies at exaggerated doses of 1OX also demonstrated no drug-related adverse effects in kittens and young adult cats.

How supplied:

INTERCEPTOR for Cats is available in three tablet sizes (see Dosage section), formulated according to the weight of the cat. Each tablet size is available in color-coded packages of 6 or 12 tablets each, which are packaged 10 per display carton.

Storage conditions:

INTERCEPTOR for Cats should be stored at room temperature, between 59° and 77°F (15-25°C).

Manufactured for: Elanco US Inc.
Greenfield, IN 46140, USA

Approved by FDA under NADA # 140-915

Interceptor, Elanco and the diagonal bar logo are trademarks of Elanco or its affiliates.

© 2021 Elanco or its affiliates

Revision date: February 2021

Elanco™

PA103156X

Principal Display Panel - Interceptor 2.3 mg Box Label

Interceptor™
(milbemycin oxime)

6
PACK

For dogs 2-10 lbs.

Contains 10
6-count cartons

Elanco™

Principal Display Panel - Interceptor 2.3 mg Carton Label

Interceptor™
(milbemycin oxime)

BROAD SPECTRUM
PARASITICIDE

Contains once-a-month flavored
tablets to prevent heartworm disease,
control adult hookworm infection,
and remove and control adult
roundworms and whipworms in
dogs and puppies.

6
PACK

For dogs 2-10 lbs.

Net contents: 6 tablets. 2.3 mg each.

Product #616159

Approved by FDA under NADA # 140-915

Keep this and all drugs out of the reach of children.

Caution: Federal (USA) law restricts this drug to use
by or on the order of a licensed veterinarian.

Elanco™

Principal Display Panel - Interceptor 5.75 mg Box Label

Interceptor™
(milbemycin oxime)

6
PACK

For dogs 11-25 lbs.

For cats 1.5-6 lbs.

Contains 10
6-count cartons

Elanco™

Principal Display Panel - Interceptor 5.75 mg Carton Label

Interceptor™
(milbemycin oxime)

BROAD SPECTRUM
PARASITICIDE

Contains once-a-month flavored
tablets to prevent heartworm disease,
control adult hookworm infection,
and remove and control adult
roundworms and whipworms in
dogs and puppies, and to prevent
heartworm disease and remove
adult hookworms and
roundworms in cats
and kittens.

6
PACK

For dogs 11-25 lbs.

For cats 1.5-6 lbs

Net contents: 6 tablets. 5.75 mg each.

Product #616160

Approved by FDA under NADA # 140-915

Keep this and all drugs out of the reach of children.

Caution: Federal (USA) law restricts this drug to use
by or on the order of a licensed veterinarian.

Elanco™

Principal Display Panel - Interceptor 11.5 mg Box Label

Interceptor™
(milbemycin oxime)

6
PACK

For dogs 26-50 lbs.

For cats 6.1-12 lbs.

Contains 10
6-count cartons

Elanco™

Principal Display Panel - Interceptor 11.5 mg Carton Label

Interceptor™
(milbemycin oxime)

BROAD SPECTRUM
PARASITICIDE

Contains once-a-month flavored
tablets to prevent heartworm disease,
control adult hookworm infection,
and remove and control adult
roundworms and whipworms in
dogs and puppies, and to prevent
heartworm disease and remove
adult hookworms and
roundworms in cats
and kittens.

6
PACK

For dogs 26-50 lbs.

For cats 6.1-12 lbs.

Net contents: 6 tablets. 11.5 mg each.

Product #616161

Approved by FDA under NADA # 140-915

Keep this and all drugs out of the reach of children.

Caution: Federal (USA) law restricts this drug to use
by or on the order of a licensed veterinarian.

Elanco™

Principal Display Panel - Interceptor 23 mg Box Label

Interceptor™
(milbemycin oxime)

6
PACK

For dogs 51-100 lbs.

For cats 12.1-25 lbs.

Contains 10
6-count cartons

Elanco™

Principal Display Panel - Interceptor 23 mg Carton Label

Interceptor™
(milbemycin oxime)

BROAD SPECTRUM
PARASITICIDE

Contains once-a-month flavored
tablets to prevent heartworm disease,
control adult hookworm infection,
and remove and control adult
roundworms and whipworms in
dogs and puppies, and to prevent
heartworm disease and remove
adult hookworms and
roundworms in cats
and kittens.

6
PACK

For dogs 51-100 lbs.

For cats 12.1-25 lbs.

Net contents: 6 tablets. 23.0 mg each.

Product #616162

Approved by FDA under NADA # 140-915

Keep this and all drugs out of the reach of children.

Caution: Federal (USA) law restricts this drug to use
by or on the order of a licensed veterinarian.

Elanco™